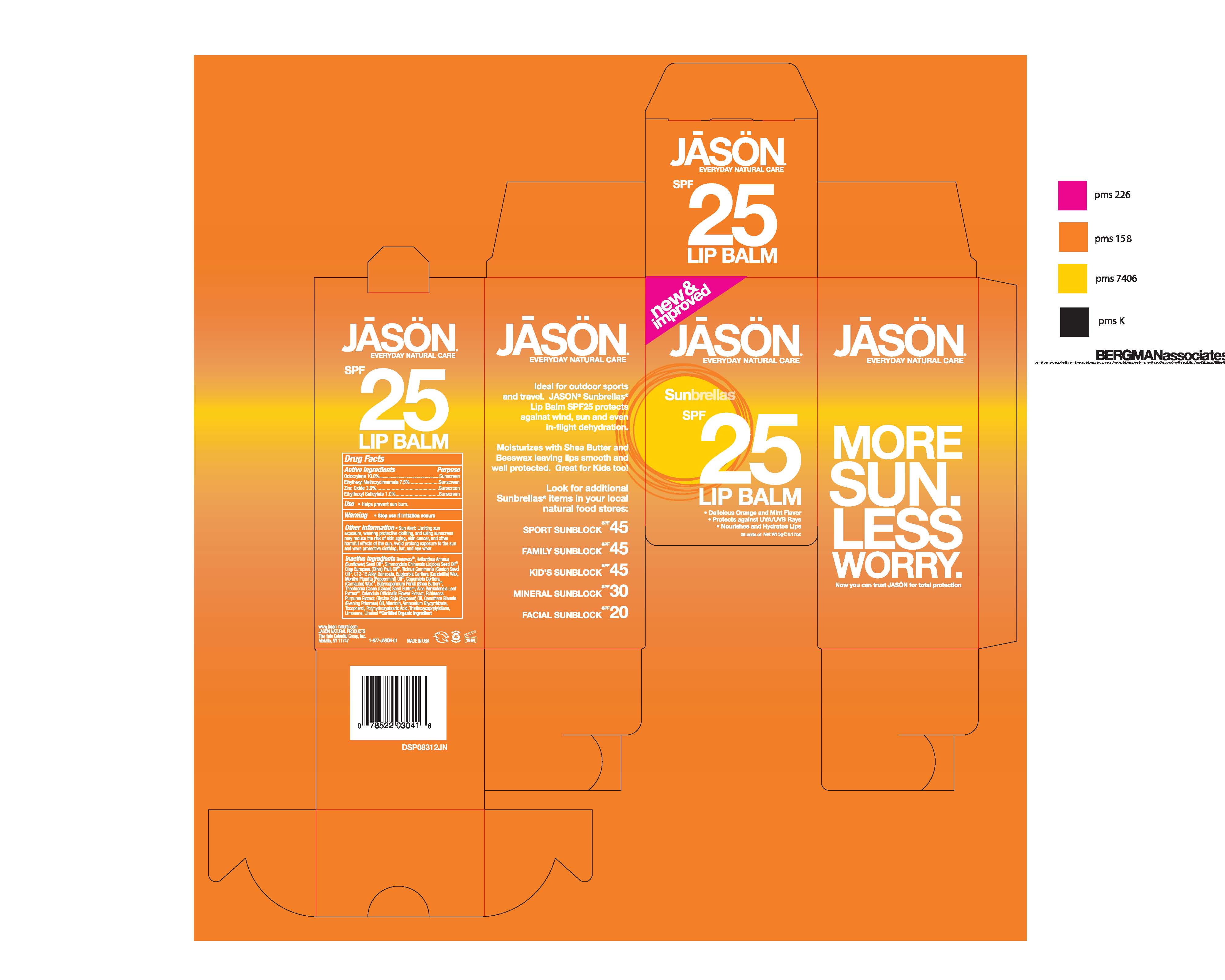 DRUG LABEL: Alba Lip Care Sunblock SPF 25
NDC: 61995-2394 | Form: CREAM
Manufacturer: The Hain Celestial Group, Inc.
Category: otc | Type: HUMAN OTC DRUG LABEL
Date: 20100726

ACTIVE INGREDIENTS: Octocrylene 10 g/100 g; Octinoxate 7.5 g/100 g; Zinc Oxide 3.9 g/100 g; Octisalate 1.0 g/100 g

Drug Facts

ACTIVE INGREDIENTS

Octocrylene 10.0%

Ethylhexyl Methoxycinnamate 7.5%

Zinc Oxide 3.9%

Ethylhexyl Salicilate 1.0%

USES

- Helps prevent sunburns
- Higher SPF gives more sunburn protection

- Apply liberally as needed 15 to 20 minutes before sun exposure

- Reapply as needed or after swimming, perspiring or towel drying

- Children under 6 months of age: ask doctor

WARNINGS

For external use only. When using this product keep out of eyes. Rinse with water to remove. Stop use and ask a doctor if rash or irritation develops and lasts. Keep out of reach of children. If swallowed, get medical help or contact Poison Center right away.

QUESTIONS?

Call (888) 659-7730 or visit www.AlbaBotanica.com

100% Vegetarian Ingredients

No Animal Testing

Alba Botanica

The Hain Celestial Group, Inc.

Melville, NY 11747

Made in the U.S.A.